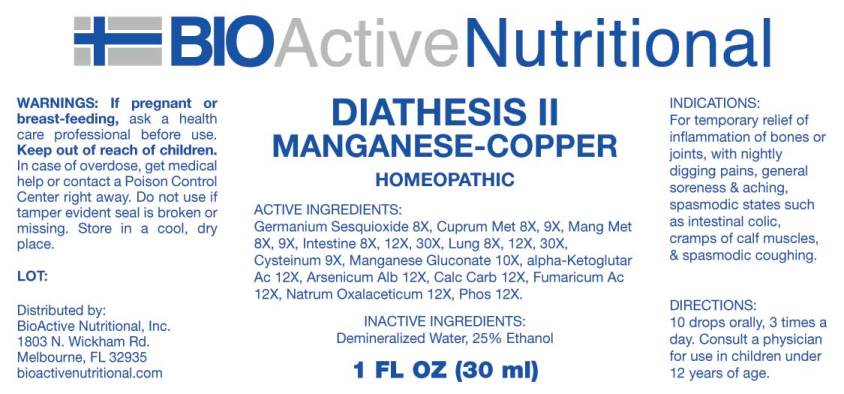 DRUG LABEL: Diathesis
NDC: 43857-0372 | Form: LIQUID
Manufacturer: BioActive Nutritional, Inc.
Category: homeopathic | Type: HUMAN OTC DRUG LABEL
Date: 20171227

ACTIVE INGREDIENTS: GERMANIUM SESQUIOXIDE 8 [hp_X]/1 mL; COPPER 8 [hp_X]/1 mL; MANGANESE 8 [hp_X]/1 mL; PORK INTESTINE 8 [hp_X]/1 mL; SUS SCROFA LUNG 8 [hp_X]/1 mL; CYSTEINE 9 [hp_X]/1 mL; MANGANESE GLUCONATE 10 [hp_X]/1 mL; OXOGLURIC ACID 12 [hp_X]/1 mL; ARSENIC TRIOXIDE 12 [hp_X]/1 mL; OYSTER SHELL CALCIUM CARBONATE, CRUDE 12 [hp_X]/1 mL; FUMARIC ACID 12 [hp_X]/1 mL; SODIUM DIETHYL OXALACETATE 12 [hp_X]/1 mL; PHOSPHORUS 12 [hp_X]/1 mL
INACTIVE INGREDIENTS: WATER; ALCOHOL

Drug Facts:

ACTIVE INGREDIENTS:

Germanium Sesquioxide 8X, Cuprum Metallicum 8X, 9X, Manganum Metallicum 8X, 9X, Intestine (Suis) 8X, 12X, 30X, Lung (Suis) 8X, 12X, 30X, Cysteinum 9X, Manganese Gluconate 10X, alpha-Ketoglutaricum Acidum 12X, Arsenicum Album 12X, Calcarea Carbonica 12X, Fumaricum Acidum 12X, Natrum Oxalaceticum 12X, Phosphorus 12X.

INDICATIONS:

For temporary relief of inflammation of bones or joints, with nightly digging pains, general soreness & aching, spasmodic states such as intestinal colic, cramps of calf muscles, & spasmodic coughing.

WARNINGS:

If pregnant or breast-feeding, ask a health care professional before use.

Keep out of reach of children. In case of overdose, get medical help or contact a Poison Control Center right away.

Do not use if tamper evident seal is broken or missing.

Store in cool, dry place.

Keep out of reach of children. In case of overdose, get medical help or contact a Poison Control Center right away.

DIRECTIONS:

10 drops orally, 3 times a day. Consult a physician for use in children under 12 years of age.

INDICATIONS:

For temporary relief of inflammation of bones or joints, with nightly digging pains, general soreness & aching, spasmodic states such as intestinal colic, cramps of calf muscles, & spasmodic coughing.

INACTIVE INGREDIENTS:

Demineralized Water, 25% Ethanol.

QUESTIONS:

Distributed by:
BioActive Nutritional, Inc.
1803 N. Wickham Rd.
Melbourne, FL 32935
bioactivenutritional.com

PACKAGE LABEL DISPLAY:

BIOActive Nutritional

DIATHESIS II

MANGANESE-COPPER

HOMEOPATHIC

1 FL OZ (30 ml)